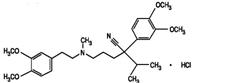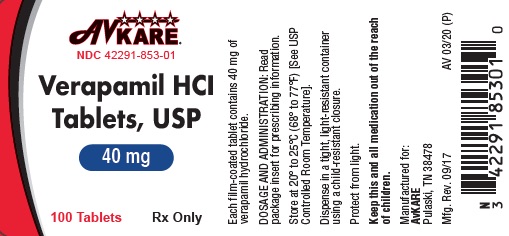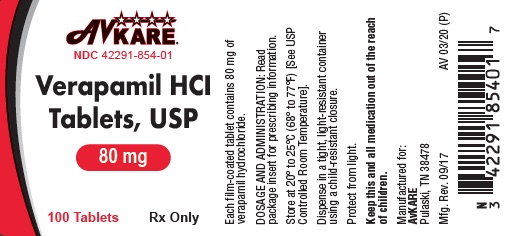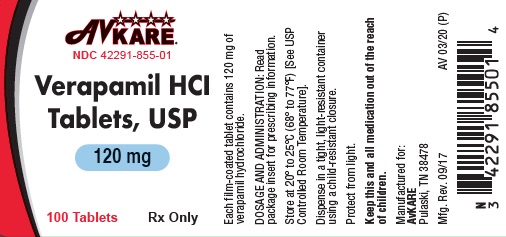 DRUG LABEL: VERAPAMIL HYDROCHLORIDE
NDC: 42291-853 | Form: TABLET
Manufacturer: AvKARE
Category: prescription | Type: HUMAN PRESCRIPTION DRUG LABEL
Date: 20260115

ACTIVE INGREDIENTS: VERAPAMIL HYDROCHLORIDE 40 mg/1 1
INACTIVE INGREDIENTS: SILICON DIOXIDE; CALCIUM PHOSPHATE, DIBASIC, DIHYDRATE; CELLULOSE, MICROCRYSTALLINE; SODIUM STARCH GLYCOLATE TYPE A POTATO; MAGNESIUM STEARATE; MINERAL OIL; SODIUM LAURYL SULFATE; TITANIUM DIOXIDE; HYPROMELLOSE 2910 (6 MPA.S)

Verapamil Hydrochloride Tablets, USP
Rx Only
These highlights do not include all the information needed to use VERAPAMIL HYDROCHLORIDE safely and effectively. See full prescribing information for VERAPAMIL HYDROCHLORIDE VERAPAMIL HYDROCHLORIDE (VERAPAMIL HYDROCHLORIDE) TABLET for ORAL use. Initial U.S. Approval:

DESCRIPTION

Verapamil hydrochloride (verapamil HCl) tablets, USP is a calcium ion influx inhibitor (slow-channel blocker or calcium ion antagonist) available for oral administration in film-coated tablets containing 40 mg, 80 mg or 120 mg of verapamil hydrochloride.

The structural formula of verapamil HCl is:

C 27 H 38 N 2 O 4 • HCl M.W. = 491.08

Benzeneacetonitrile, a-[3-[[2-(3,4-dimethoxyphenyl)ethyl] methylamino]propyl]-3,4-dimethoxy-a-(1-methylethyl) hydrochloride

Verapamil HCl is an almost white, crystalline powder, practically free of odor, with a bitter taste. It is soluble in water, chloroform, and methanol. Verapamil HCl is not chemically related to other cardioactive drugs.

Inactive ingredients include colloidal silicon dioxide, dibasic calcium phosphate dihydrate, magnesium stearate, microcrystalline cellulose, sodium starch glycolate, light mineral oil, sodium lauryl sulfate, titanium dioxide and hypromellose.

CLINICAL PHARMACOLOGY

Verapamil hydrochloride is a calcium ion influx inhibitor (slow-channel blocker or calcium ion antagonist) that exerts its pharmacologic effects by modulating the influx of ionic calcium across the cell membrane of the arterial smooth muscle as well as in conductile and contractile myocardial cells.

Mechanism of Action

Angina: The precise mechanism of action of verapamil hydrochloride as an antianginal agent remains to be fully determined, but includes the following two mechanisms:

1. Relaxation and prevention of coronary artery spasm: Verapamil hydrochloride dilates the main coronary arteries and coronary arterioles, both in normal and ischemic regions, and is a potent inhibitor of coronary artery spasm, whether spontaneous or ergonovine-induced. This property increases myocardial oxygen delivery in patients with coronary artery spasm and is responsible for the effectiveness of verapamil hydrochloride in vasospastic (Prinzmetal's or variant) as well as unstable angina at rest. Whether this effect plays any role in classical effort angina is not clear, but studies of exercise tolerance have not shown an increase in the maximum exercise rate-pressure product, a widely accepted measure of oxygen utilization. This suggests that, in general, relief of spasm or dilation of coronary arteries is not an important factor in classical angina.

2. Reduction of oxygen utilization: Verapamil hydrochloride regularly reduces the total peripheral resistance (afterload) against which the heart works both at rest and at a given level of exercise by dilating peripheral arterioles. This unloading of the heart reduces myocardial energy consumption and oxygen requirements and probably accounts for the effectiveness of verapamil hydrochloride in chronic stable effort angina.

Arrhythmia: Electrical activity through the AV node depends, to a significant degree, upon calcium influx through the slow channel. By decreasing the influx of calcium, verapamil hydrochloride prolongs the effective refractory period within the AV node and slows AV conduction in a rate-related manner. This property accounts for the ability of verapamil hydrochloride to slow the ventricular rate in patients with chronic atrial flutter or atrial fibrillation.

Normal sinus rhythm is usually not affected, but in patients with sick sinus syndrome, verapamil hydrochloride may interfere with sinus-node impulse generation and may induce sinus arrest or sinoatrial block. Atrioventricular block can occur in patients without preexisting conduction defects (see WARNINGS). Verapamil hydrochloride decreases the frequency of episodes of paroxysmal supraventricular tachycardia.

Verapamil hydrochloride does not alter the normal atrial action potential or intraventricular conduction time, but in depressed atrial fibers it decreases amplitude, velocity of depolarization, and conduction velocity. Verapamil hydrochloride may shorten the antegrade effective refractory period of the accessory bypass tract. Acceleration of ventricular rate and/or ventricular fibrillation has been reported in patients with atrial flutter or atrial fibrillation and a coexisting accessory AV pathway following administration of verapamil (see WARNINGS).

Verapamil hydrochloride has a local anesthetic action that is 1.6 times that of procaine on an equimolar basis. It is not known whether this action is important at the doses used in man.

Essential hypertension: Verapamil hydrochloride exerts antihypertensive effects by decreasing systemic vascular resistance, usually without orthostatic decreases in blood pressure or reflex tachycardia; bradycardia (rate less than 50 beats/min) is uncommon (1.4%). During isometric or dynamic exercise, verapamil hydrochloride does not alter systolic cardiac function in patients with normal ventricular function.

Verapamil hydrochloride does not alter total serum calcium levels. However, one report suggested that calcium levels above the normal range may alter the therapeutic effect of Verapamil hydrochloride.

Pharmacokinetics and metabolism: More than 90% of the orally administered dose of Verapamil hydrochloride is absorbed. Because of rapid biotransformation of verapamil during its first pass through the portal circulation, bioavailability ranges from 20% to 35%. Peak plasma concentrations are reached between 1 and 2 hours after oral administration. Chronic oral administration of 120 mg of verapamil HCl every 6 hours resulted in plasma levels of verapamil ranging from 125 to 400 ng/ml, with higher values reported occasionally. A nonlinear correlation between the verapamil dose administered and verapamil plasma levels does exist. No relationship has been established between the plasma concentration of verapamil and a reduction in blood pressure. In early dose titration with verapamil, a relationship exists between verapamil plasma concentration and prolongation of the PR interval. However, during chronic administration this relationship may disappear. The mean elimination half-life in single-dose studies ranged from 2.8 to 7.4 hours. In these same studies, after repetitive dosing, the half-life increased to a range from 4.5 to 12.0 hours (after less than 10 consecutive doses given 6 hours apart). Half-life of verapamil may increase during titration. Aging may affect the pharmacokinetics of verapamil. Elimination half-life may be prolonged in the elderly. In healthy men, orally administered verapamil hydrochloride undergoes extensive metabolism in the liver. Twelve metabolites have been identified in plasma; all except norverapamil are present in trace amounts only.

Norverapamil can reach steady-state plasma concentrations approximately equal to those of verapamil itself. The cardiovascular activity of norverapamil appears to be approximately 20% that of verapamil. Approximately 70% of an administered dose is excreted as metabolites in the urine and 16% or more in the feces within 5 days. About 3% to 4% is excreted in the urine as unchanged drug. Approximately 90% is bound to plasma proteins. In patients with hepatic insufficiency, metabolism is delayed and elimination half-life prolonged up to 14 to 16 hours (see PRECAUTIONS); the volume of distribution is increased and plasma clearance reduced to about 30% of normal. Verapamil clearance values suggest that patients with liver dysfunction may attain therapeutic verapamil plasma concentrations with one third of the oral daily dose required for patients with normal liver function.

After four weeks of oral dosing (120 mg q.i.d.), verapamil and norverapamil levels were noted in the cerebrospinal fluid with estimated partition coefficient of 0.06 for verapamil and 0.04 for norverapamil.

Hemodynamics and myocardial metabolism: Verapamil hydrochloride reduces afterload and myocardial contractility. Improved left ventricular diastolic function in patients with Idiopathic Hypertrophic Subaortic Stenosis (IHSS) and those with coronary heart disease has also been observed with verapamil hydrochloride therapy. In most patients, including those with organic cardiac disease, the negative inotropic action of verapamil hydrochloride is countered by reduction of afterload, and cardiac index is usually not reduced. However, in patients with severe left ventricular dysfunction (e.g., pulmonary wedge pressure above 20 mm Hg or ejection fraction less than 30%), or in patients taking beta-adrenergic blocking agents or other cardiodepressant drugs, deterioration of ventricular function may occur (see PRECAUTIONS, Drug interactions).

Pulmonary function: Verapamil hydrochloride does not induce bronchoconstriction and, hence, does not impair ventilatory function.

INDICATIONS AND USAGE

Verapamil hydrochloride tablets USP are indicated for the treatment of the following:

Angina

1.Angina at rest including:

-Vasospastic (Prinzmetal's variant) angina

-Unstable (crescendo, pre-infarction) angina

2.Chronic stable angina (classic effort-associated angina)

Arrhythmias

1.In association with digitalis for the control of ventricular rate at rest and during stress in patients with chronic atrial flutter and/or atrial fibrillation (see WARNINGS: Accessory bypass tract)

2.Prophylaxis of repetitive paroxysmal supraventricular tachycardia

Essential hypertension

Verapamil hydrochloride is indicated for the treatment of hypertension, to lower blood pressure. Lowering blood pressure reduces the risk of fatal and nonfatal cardiovascular events, primarily strokes and myocardial infarctions. These benefits have been seen in controlled trials of antihypertensive drugs from a wide variety of pharmacologic classes, including this drug.

Control of high blood pressure should be part of comprehensive cardiovascular risk management, including, as appropriate, lipid control, diabetes management, antithrombotic therapy, smoking cessation, exercise, and limited sodium intake. Many patients will require more than one drug to achieve blood pressure goals. For specific advice on goals and management, see published guidelines, such as those of the National High Blood Pressure Education Program's Joint National Committee on Prevention, Detection, Evaluation, and Treatment of High Blood Pressure (JNC).

Numerous antihypertensive drugs, from a variety of pharmacologic classes and with different mechanisms of action, have been shown in randomized controlled trials to reduce cardiovascular morbidity and mortality, and it can be concluded that it is blood pressure reduction, and not some other pharmacologic property of the drugs, that is largely responsible for those benefits. The largest and most consistent cardiovascular outcome benefit has been a reduction in the risk of stroke, but reductions in myocardial infarction and cardiovascular mortality also have been seen regularly.

Elevated systolic or diastolic pressure causes increased cardiovascular risk, and the absolute risk increase per mmHg is greater at higher blood pressures, so that even modest reductions of severe hypertension can provide substantial benefit. Relative risk reduction from blood pressure reduction is similar across populations with varying absolute risk, so the absolute benefit is greater in patients who are at higher risk independent of their hypertension (for example, patients with diabetes or hyperlipidemia), and such patients would be expected to benefit from more aggressive treatment to a lower blood pressure goal.

Some antihypertensive drugs have smaller blood pressure effects (as monotherapy) in black patients, and many antihypertensive drugs have additional approved indications and effects (e.g., on angina, heart failure, or diabetic kidney disease). These considerations may guide selection of therapy.

CONTRAINDICATIONS

Verapamil HCl tablets are contraindicated in:

1.Severe left ventricular dysfunction (see WARNINGS)

2.Hypotension (systolic pressure less than 90 mm Hg) or cardiogenic shock

3.Sick sinus syndrome (except in patients with a functioning artificial ventricular pacemaker)

4.Second-or third-degree AV block (except in patients with a functioning artificial ventricular pacemaker)

5.Patients with atrial flutter or atrial fibrillation and an accessory bypass tract (e.g., Wolff-Parkinson-White, Lown-Ganong-Levine syndromes) (see WARNINGS)

6.Patients with known hypersensitivity to verapamil hydrochloride

WARNINGS

Heart failure: Verapamil has a negative inotropic effect, which in most patients is compensated by its afterload reduction (decreased systemic vascular resistance) properties without a net impairment of ventricular performance. In clinical experience with 4,954 patients, 87 (1.8%) developed congestive heart failure or pulmonary edema. Verapamil should be avoided in patients with severe left ventricular dysfunction (e.g., ejection fraction less than 30%) or moderate to severe symptoms of cardiac failure and in patients with any degree of ventricular dysfunction if they are receiving a beta-adrenergic blocker (see PRECAUTIONS, Drug interactions). Patients with milder ventricular dysfunction should, if possible, be controlled with optimum doses of digitalis and/or diuretics before verapamil treatment. (Note interactions with digoxin under PRECAUTIONS)

Hypotension: Occasionally, the pharmacologic action of verapamil may produce a decrease in blood pressure below normal levels, which may result in dizziness or symptomatic hypotension. The incidence of hypotension observed in 4,954 patients enrolled in clinical trials was 2.5%. In hypertensive patients, decreases in blood pressure below normal are unusual. Tilt-table testing (60 degrees) was not able to induce orthostatic hypotension.

Elevated liver enzymes: Elevations of transaminases with and without concomitant elevations in alkaline phosphatase and bilirubin have been reported. Such elevations have sometimes been transient and may disappear even with continued verapamil treatment. Several cases of hepatocellular injury related to verapamil have been proven by rechallenge; half of these had clinical symptoms (malaise, fever, and/or right upper quadrant pain), in addition to elevation of SGOT, SGPT, and alkaline phosphatase. Periodic monitoring of liver function in patients receiving verapamil is therefore prudent.

Accessory bypass tract (Wolff-Parkinson-White or Lown-Ganong-Levine): Some patients with paroxysmal and/or chronic atrial fibrillation or atrial flutter and a coexisting accessory AV pathway have developed increased antegrade conduction across the accessory pathway bypassing the AV node, producing a very rapid ventricular response or ventricular fibrillation after receiving intravenous verapamil (or digitalis). Although a risk of this occurring with oral verapamil has not been established, such patients receiving oral verapamil may be at risk and its use in these patients is contraindicated (see CONTRAINDICATIONS). Treatment is usually DC-cardioversion. Cardioversion has been used safely and effectively after oral verapamil hydrochloride.

Atrioventricular block: The effect of verapamil on AV conduction and the SA node may cause asymptomatic first-degree AV block and transient bradycardia, sometimes accompanied by nodal escape rhythms. PR-interval prolongation is correlated with verapamil plasma concentrations especially during the early titration phase of therapy. Higher degrees of AV block, however, were infrequently (0.8%) observed. Marked first-degree block or progressive development to second-or third-degree AV block requires a reduction in dosage or, in rare instances, discontinuation of verapamil HCl and institution of appropriate therapy, depending on the clinical situation.

Patients with hypertrophic cardiomyopathy (IHSS): In 120 patients with hypertrophic cardiomyopathy (most of them refractory or intolerant to propranolol) who received therapy with verapamil at doses up to 720 mg/day, a variety of serious adverse effects were seen. Three patients died in pulmonary edema; all had severe left ventricular outflow obstruction and a past history of left ventricular dysfunction. Eight other patients had pulmonary edema and/or severe hypotension; abnormally high (greater than 20 mm Hg) pulmonary wedge pressure and a marked left ventricular outflow obstruction were present in most of these patients. Concomitant administration of quinidine (see PRECAUTIONS, Drug interactions) preceded the severe hypotension in 3 of the 8 patients (2 of whom developed pulmonary edema). Sinus bradycardia occurred in 11% of the patients, second-degree AV block in 4%, and sinus arrest in 2%. It must be appreciated that this group of patients had a serious disease with a high mortality rate. Most adverse effects responded well to dose reduction, and only rarely did verapamil use have to be discontinued.

PRECAUTIONS

General

Use in patients with impaired hepatic function: Since verapamil is highly metabolized by the liver, it should be administered cautiously to patients with impaired hepatic function. Severe liver dysfunction prolongs the elimination half-life of verapamil to about 14 to 16 hours; hence, approximately 30% of the dose given to patients with normal liver function should be administered to these patients. Careful monitoring for abnormal prolongation of the PR interval or other signs of excessive pharmacologic effects (see OVERDOSAGE) should be carried out.

Use in patients with attenuated (decreased) neuromuscular transmission: It has been reported that verapamil decreases neuromuscular transmission in patients with Duchenne's muscular dystrophy, and that verapamil prolongs recovery from the neuromuscular blocking agent vecuronium, and causes a worsening of myasthenia gravis. It may be necessary to decrease the dosage of verapamil when it is administered to patients with attenuated neuromuscular transmission.

Use in patients with impaired renal function: About 70% of an administered dose of verapamil is excreted as metabolites in the urine. Verapamil is not removed by hemodialysis. Until further data are available, verapamil should be administered cautiously to patients with impaired renal function. These patients should be carefully monitored for abnormal prolongation of the PR interval or other signs of overdosage (see OVERDOSAGE).

Drug Interactions

Cytochrome inducers/inhibitors: In vitro metabolic studies indicate that verapamil is metabolized by cytochrome P450 CYP3A4, CYP1A2, CYP2C8, CYP2C9 and CYP2C18. Clinically significant interactions have been reported with inhibitors of CYP3A4 (e.g., erythromycin, ritonavir) causing elevation of plasma levels of verapamil while inducers of CYP3A4 (e.g., rifampin) have caused a lowering of plasma levels of verapamil.

HMG-CoA reductase inhibitors: The use of HMG-CoA reductase inhibitors that are CYP3A4 substrates in combination with verapamil has been associated with reports of myopathy/rhabdomyolysis.

Co-administration of multiple doses of 10 mg of verapamil with 80 mg simvastatin resulted in exposure to simvastatin 2.5-fold that following simvastatin alone. Limit the dose of simvastatin in patients on verapamil to 10 mg daily. Limit the daily dose of lovastatin to 40 mg. Lower starting and maintenance doses of other CYP3A4 substrates (e.g., atorvastatin) may be required as verapamil may increase the plasma concentration of these drugs.

Ivabradine: Concurrent use of verapamil increases exposure to ivabradine and may exacerbate bradycardia and conduction disturbances. Avoid co-administration of verapamil and ivabradine.

Aspirin: In a few reported cases, co-administration of verapamil with aspirin has led to increased bleeding times greater than observed with aspirin alone.

Grapefruit juice: Grapefruit juice may increase plasma levels of verapamil.

Alcohol: Verapamil may increase blood alcohol concentrations and prolong its effects.

Beta-blockers: Controlled studies in small numbers of patients suggest that the concomitant use of verapamil hydrochloride and oral beta-adrenergic blocking agents may be beneficial in certain patients with chronic stable angina or hypertension, but available information is not sufficient to predict with confidence the effects of concurrent treatment in patients with left ventricular dysfunction or cardiac conduction abnormalities. Concomitant therapy with beta-adrenergic blockers and verapamil may result in additive negative effects on heart rate, atrioventricular conduction and/or cardiac contractility.

In one study involving 15 patients treated with high doses of propranolol (median dose: 480 mg/day; range: 160 to 1,280 mg/day) for severe angina, with preserved left ventricular function (ejection fraction greater than 35%), the hemodynamic effects of additional therapy with verapamil HCl were assessed using invasive methods. The addition of verapamil to high-dose beta-blockers induced modest negative inotropic and chronotropic effects that were not severe enough to limit short-term (48 hours) combination therapy in this study. These modest cardiodepressant effects persisted for greater than 6 but less than 30 hours after abrupt withdrawal of beta-blockers and were closely related to plasma levels of propranolol. The primary verapamil/beta-blocker interaction in this study appeared to be hemodynamic rather than electrophysiologic.

In other studies, verapamil did not generally induce significant negative inotropic, chronotropic, or dromotropic effects in patients with preserved left ventricular function receiving low or moderate doses of propranolol (less than or equal to 320 mg/day); in some patients, however, combined therapy did produce such effects. Therefore, if combined therapy is used, close surveillance of clinical status should be carried out. Combined therapy should usually be avoided in patients with atrioventricular conduction abnormalities and those with depressed left ventricular function.

Asymptomatic bradycardia (36 beats/min) with a wandering atrial pacemaker has been observed in a patient receiving concomitant timolol (a beta-adrenergic blocker) eyedrops and oral verapamil.

A decrease in metoprolol and propranolol clearance has been observed when either drug is administered concomitantly with verapamil. A variable effect has been seen when verapamil and atenolol were given together.

Digitalis: Clinical use of verapamil in digitalized patients has shown the combination to be well tolerated if digoxin doses are properly adjusted. However, chronic verapamil treatment can increase serum digoxin levels by 50% to 75% during the first week of therapy, and this can result in digitalis toxicity. In patients with hepatic cirrhosis, the influence of verapamil on digoxin kinetics is magnified. Verapamil may reduce total body clearance and extrarenal clearance of digitoxin by 27% and 29%, respectively. Maintenance and digitalization doses should be reduced when verapamil is administered, and the patient should be reassessed to avoid over-or under-digitalization. Whenever over-digitalization is suspected, the daily dose of digitalis should be reduced or temporarily discontinued. On discontinuation of verapamil hydrochloride use, the patient should be reassessed to avoid under-digitalization.

Antihypertensive agents: Verapamil administered concomitantly with oral antihypertensive agents (e.g., vasodilators, angiotensin-converting enzyme inhibitors, diuretics, beta-blockers) will usually have an additive effect on lowering blood pressure. Patients receiving these combinations should be appropriately monitored. Concomitant use of agents that attenuate alpha-adrenergic function with verapamil may result in a reduction in blood pressure that is excessive in some patients. Such an effect was observed in one study following the concomitant administration of verapamil and prazosin.

Antiarrhythmic agents:

Disopyramide: Until data on possible interactions between verapamil and disopyramide are obtained, disopyramide should not be administered within 48 hours before or 24 hours after verapamil administration.

Flecainide: A study in healthy volunteers showed that the concomitant administration of flecainide and verapamil may have additive effects on myocardial contractility, AV conduction, and repolarization. Concomitant therapy with flecainide and verapamil may result in additive negative inotropic effect and prolongation of atrioventricular conduction.

Quinidine: In a small number of patients with hypertrophic cardiomyopathy (IHSS), concomitant use of verapamil and quinidine resulted in significant hypotension. Until further data are obtained, combined therapy of verapamil and quinidine in patients with hypertrophic cardiomyopathy should probably be avoided.

The electrophysiologic effects of quinidine and verapamil on AV conduction were studied in 8 patients. Verapamil significantly counteracted the effects of quinidine on AV conduction. There has been a report of increased quinidine levels during verapamil therapy.

Other agents:

Nitrates: Verapamil has been given concomitantly with short-and long-acting nitrates without any undesirable drug interactions. The pharmacologic profile of both drugs and the clinical experience suggest beneficial interactions.

Cimetidine: The interaction between cimetidine and chronically administered verapamil has not been studied. Variable results on clearance have been obtained in acute studies of healthy volunteers; clearance of verapamil was either reduced or unchanged.

Lithium: Increased sensitivity to the effects of lithium (neurotoxicity) has been reported during concomitant verapamil-lithium therapy; lithium levels have been observed sometimes to increase, sometimes to decrease, and sometimes to be unchanged. Patients receiving both drugs must be monitored carefully.

Carbamazepine: Verapamil therapy may increase carbamazepine concentrations during combined therapy. This may produce carbamazepine side effects such as diplopia, headache, ataxia, or dizziness.

Rifampin: Therapy with rifampin may markedly reduce oral verapamil bioavailability.

Phenobarbital: Phenobarbital therapy may increase verapamil clearance.

Cyclosporine: Verapamil therapy may increase serum levels of cyclosporine.

Theophylline: Verapamil may inhibit the clearance and increase the plasma levels of theophylline.

Inhalation anesthetics: Animal experiments have shown that inhalation anesthetics depress cardiovascular activity by decreasing the inward movement of calcium ions. When used concomitantly, inhalation anesthetics and calcium antagonists, such as verapamil, should each be titrated carefully to avoid excessive cardiovascular depression.

Neuromuscular blocking agents: Clinical data and animal studies suggest that verapamil may potentiate the activity of neuromuscular blocking agents (curare-like and depolarizing). It may be necessary to decrease the dose of verapamil and/or the dose of the neuromuscular blocking agent when the drugs are used concomitantly.

Telithromycin: Hypotension and bradyarrhythmias have been observed in patients receiving concurrent telithromycin, an antibiotic in the ketolide class.

Clonidine: Sinus bradycardia resulting in hospitalization and pacemaker insertion has been reported in association with the use of clonidine concurrently with verapamil. Monitor heart rate in patients receiving concomitant verapamil and clonidine.

Mammalian target of rapamycin (mTOR) inhibitors: In a study of 25 healthy volunteers with co-administration of verapamil with sirolimus, whole blood sirolimus C max and AUC were increased 130% and 120%, respectively. Plasma S-(-) verapamil C max and AUC were both increased 50%. Co-administration of verapamil with everolimus in 16 healthy volunteers increased the C max and AUC of everolimus by 130% and 250%, respectively. With concomitant use of mTOR inhibitors (e.g., sirolimus, temsirolimus, and everolimus) and verapamil, consider appropriate dose reductions of both medications.

Carcinogenesis, Mutagenesis, Impairment of Fertility

An 18-month toxicity study in rats, at a low multiple (6-fold) of the maximum recommended human dose, and not the maximum tolerated dose, did not suggest a tumorigenic potential. There was no evidence of a carcinogenic potential of verapamil administered in the diet of rats for two years at doses of 10, 35, and 120 mg/kg/day or approximately 1, 3.5, and 12 times, respectively, the maximum recommended human daily dose (480 mg/day or 9.6 mg/kg/day).

Verapamil was not mutagenic in the Ames test in 5 test strains at 3 mg per plate with or without metabolic activation.

Studies in female rats at daily dietary doses up to 5.5 times (55 mg/kg/day) the maximum recommended human dose did not show impaired fertility. Effects on male fertility have not been determined.

Pregnancy

Pregnancy Category C. Reproduction studies have been performed in rabbits and rats at oral doses up to 1.5 (15 mg/kg/day) and 6 (60 mg/kg/day) times the human oral daily dose, respectively, and have revealed no evidence of teratogenicity. In the rat, however, this multiple of the human dose was embryocidal and retarded fetal growth and development, probably because of adverse maternal effects reflected in reduced weight gains of the dams. This oral dose has also been shown to cause hypotension in rats. There are no adequate and well-controlled studies in pregnant women. Because animal reproduction studies are not always predictive of human response, this drug should be used during pregnancy only if clearly needed. Verapamil crosses the placental barrier and can be detected in umbilical vein blood at delivery.

Labor and Delivery

It is not known whether the use of verapamil during labor or delivery has immediate or delayed adverse effects on the fetus, or whether it prolongs the duration of labor or increases the need for forceps delivery or other obstetric intervention. Such adverse experiences have not been reported in the literature, despite a long history of use of verapamil in Europe in the treatment of cardiac side effects of beta-adrenergic agonist agents used to treat premature labor.

Nursing Mothers

Verapamil is excreted in human milk. Because of the potential for adverse reactions in nursing infants from verapamil, nursing should be discontinued while verapamil is administered.

Pediatric Use

Safety and effectiveness in pediatric patients have not been established.

ANIMAL PHARMACOLOGY & OR TOXICOLOGY

In chronic animal toxicology studies, verapamil caused lenticular and/or suture line changes at 30 mg/kg/day or greater, and frank cataracts at 62.5 mg/kg/day or greater in the beagle dog but not in the rat. Development of cataracts due to verapamil has not been reported in man.

ADVERSE REACTIONS

Serious adverse reactions are uncommon when verapamil hydrochloride therapy is initiated with upward dose titration within the recommended single and total daily dose. See WARNINGS for discussion of heart failure, hypotension, elevated liver enzymes, AV block, and rapid ventricular response. Reversible (upon discontinuation of verapamil) non-obstructive, paralytic ileus has been infrequently reported in association with the use of verapamil. The following reactions to orally administered verapamil occurred at rates greater than 1.0% or occurred at lower rates but appeared clearly drug-related in clinical trials in 4,954 patients:

Constipation | 7.30% | Dyspnea | 1.40%
Dizziness | 3.30% | Bradycardia (HR <50/min) | 1.40%
Nausea | 2.70% | AV block total (1°, 2°, 3°) | 1.20%
Hypotension | 2.50% | 2° and 3° | 0.80%
Headache | 2.20% | Rash | 1.20%
Edema | 1.90% | Flushing | 0.60%
CHF, Pulmonary edema | 1.80%
Fatigue | 1.70%
Elevated liver enzymes (see WARNINGS)

In clinical trials related to the control of ventricular response in digitalized patients who had atrial fibrillation or flutter, ventricular rates below 50 at rest occurred in 15% of patients and asymptomatic hypotension occurred in 5% of patients.

The following reactions, reported in 1.0% or less of patients, occurred under conditions (open trials, marketing experience) where a causal relationship is uncertain; they are listed to alert the physician to a possible relationship:

Cardiovascular: angina pectoris, atrioventricular dissociation, chest pain, claudication, myocardial infarction, palpitations, purpura (vasculitis), syncope.

Digestive system : diarrhea, dry mouth, gastrointestinal distress, gingival hyperplasia.

Hemic and lymphatic: ecchymosis or bruising.

Nervous system: cerebrovascular accident, confusion, equilibrium disorders, insomnia, muscle cramps, paresthesia, psychotic symptoms, shakiness, somnolence, extrapyramidal symptoms.

Skin: arthralgia and rash, exanthema, hair loss, hyperkeratosis, macules, sweating, urticaria, Stevens-Johnson syndrome, erythema multiforme.

Special senses: blurred vision, tinnitus.

Urogenital: gynecomastia, galactorrhea/hyperprolactinemia, increased urination, spotty menstruation, impotence.

Treatment of acute cardiovascular adverse reactions: The frequency of cardiovascular adverse reactions that require therapy is rare; hence, experience with their treatment is limited. Whenever severe hypotension or complete AV block occurs following oral administration of verapamil, the appropriate emergency measures should be applied immediately; e.g., intravenously administered norepinephrine bitartrate, atropine sulfate, isoproterenol HCl (all in the usual doses), or calcium gluconate (10% solution). In patients with hypertrophic cardiomyopathy (IHSS), alphaadrenergic agents (phenylephrine HCl, metaraminol bitartrate, or methoxamine HCl) should be used to maintain blood pressure, and isoproterenol and norepinephrine should be avoided. If further support is necessary, dopamine HCl or dobutamine HCl may be administered. Actual treatment and dosage should depend on the severity of the clinical situation and the judgment and experience of the treating physician.

To report SUSPECTED ADVERSE REACTIONS contact AvKARE at 1-855-361-3993; email drugsafety@avkare.com; or FDA at 1-800-FDA-1088 or www.fda.gov/medwatch.

OVERDOSAGE

Treat all verapamil overdoses as serious and maintain observation for at least 48 hours (especially Verapamil Hydrochloride Tablets SR), preferably under continuous hospital care. Delayed pharmacodynamic consequences may occur with the sustained-release formulation. Verapamil is known to decrease gastrointestinal transit time.

Treatment of overdosage should be supportive. Beta-adrenergic stimulation or parenteral administration of calcium solutions may increase calcium ion flux across the slow channel and have been used effectively in treatment of deliberate overdosage with verapamil. In a few reported cases, overdose with calcium channel blockers has been associated with hypotension and bradycardia, initially refractory to atropine but becoming more responsive to this treatment when the patients received large doses (close to 1 gram/ hour for more than 24 hours) of calcium chloride. Verapamil cannot be removed by hemodialysis. Clinically significant hypotensive reactions or high degree AV block should be treated with vasopressor agents or cardiac pacing, respectively. Asystole should be handled by the usual measures including cardiopulmonary resuscitation.

DOSAGE AND ADMINISTRATION

The dose of verapamil must be individualized by titration. The usefulness and safety of dosages exceeding 480 mg/day have not been established; therefore, this daily dosage should not be exceeded. Since the half-life of verapamil increases during chronic dosing, maximum response may be delayed.

Angina: Clinical trials show that the usual dose is 80 mg to 120 mg three times a day. However, 40 mg three times a day may be warranted in patients who may have an increased response to verapamil (e.g., decreased hepatic function, elderly, etc). Upward titration should be based on therapeutic efficacy and safety evaluated approximately eight hours after dosing. Dosage may be increased at daily (e.g., patients with unstable angina) or weekly intervals until optimum clinical response is obtained.

Arrhythmias: The dosage in digitalized patients with chronic atrial fibrillation (see PRECAUTIONS) ranges from 240 to 320 mg/day in divided (t.i.d. or q.i.d.) doses. The dosage for prophylaxis of PSVT (non-digitalized patients) ranges from 240 to 480 mg/day in divided (t.i.d. or q.i.d.) doses. In general, maximum effects for any given dosage will be apparent during the first 48 hours of therapy.

Essential hypertension: Dose should be individualized by titration. The usual initial monotherapy dose in clinical trials was 80 mg three times a day (240 mg/ day). Daily dosages of 360 and 480 mg have been used but there is no evidence that dosages beyond 360 mg provided added effect. Consideration should be given to beginning titration at 40 mg three times per day in patients who might respond to lower doses, such as the elderly or people of small stature. The antihypertensive effects of verapamil hydrochloride are evident within the first week of therapy. Upward titration should be based on therapeutic efficacy, assessed at the end of the dosing interval.

HOW SUPPLIED

Verapamil Hydrochloride Tablets, USP 120 mg tablets are round, standard concave, white film-coated, scored, debossed "HP" above and "27" below on one side and plain on the reverse side, supplied as:

42291-855-01 bottle of 100

Verapamil Hydrochloride Tablets, USP 80 mg tablets are round, standard concave, white film-coated, scored, debossed "HP" above and "26" below on one side and plain on the reverse side, supplied as:

42291-854-01 bottle of 100

Verapamil Hydrochloride Tablets, USP 40 mg tablets are round, white film-coated, debossed "HP59" on one side and plain on the reverse side, supplied as:

42291-853-01 bottle of 100

Store at 20° to 25°C (68° to 77°F) [See USP controlled room temperature] and protect from light. Dispense in a tight, light-resistant container using a child-resistant closure.

Manufactured for:

AvKARE

Pulaski, TN 38478

Mfg. Iss. 06/18

AV 03/20 (P)